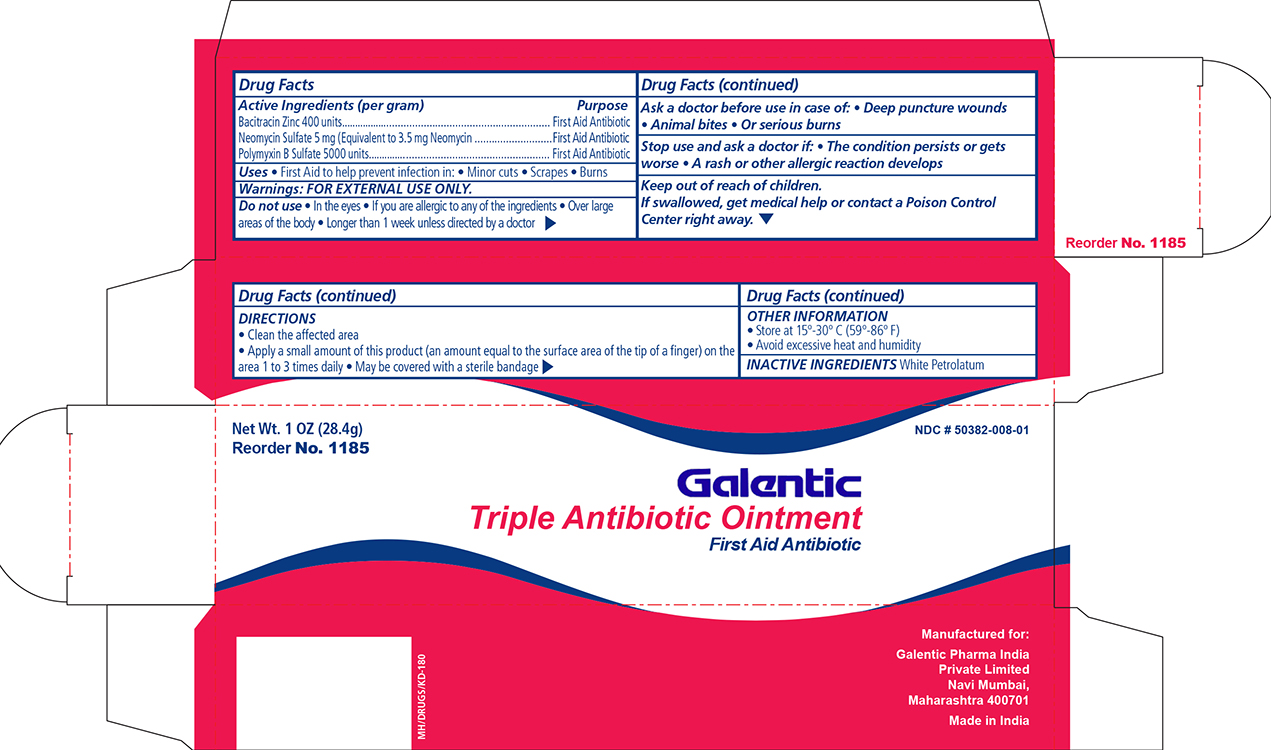 DRUG LABEL: bacitracin zinc, neomycin sulfate and polymyxin b sulfate
NDC: 50382-008 | Form: OINTMENT
Manufacturer: Galentic Pharma (India) Private Limited
Category: otc | Type: HUMAN OTC DRUG LABEL
Date: 20130807

ACTIVE INGREDIENTS: BACITRACIN ZINC 400 [iU]/1 g; NEOMYCIN SULFATE 5 mg/1 g; POLYMYXIN B SULFATE 5000 [iU]/1 g
INACTIVE INGREDIENTS: PETROLATUM

Galentic Triple Antibiotic Ointment

Active ingredient (in ea. gram) Purpose
Bacitracin Zinc 400 Units First Aid Antibiotic

Neomyxin Sulfate 5mg (Equivalent to 3.5 mg Neomyxin) First Aid Antibiotic

Polymyxin B Sulfate 5000 Units First Aid Antibiotic

Purpose:

First aid to help prevent infection in:

- Minor cuts
- scrapes
- burns

Indications and Usage:

- in case of deep or puncture wounds
- animal bites
- serious burns

Other information

- store at controlled room temperature 15°-30° C (59°-86° F)
- avoid excessive heat and humidity

Inactive ingredients:

Hard Paraffin, Liquid Paraffin, White Soft Paraffin

Keep Out Of Reach Of Children

Warnings

For external use only

Dosage and Administration

- clean the affected areas
- apply a small amount of product (an amount equal to the surface area of the tip of the finger) on the area 1 to 3 times daily
- may be covered with a sterile bandage

Do Not Use:

- if you are allergic to any of the ingredients
- in the eyes
- over large areas of the body
- longer than 1 week unless directed by a doctor

- Stop use and ask a doctor if condition persists or gets worse, or if a rash or other allergic reaction occurs

Principal Display Panel

Galentic Triple Antibiotic Ointment

Gal Triple.jpg